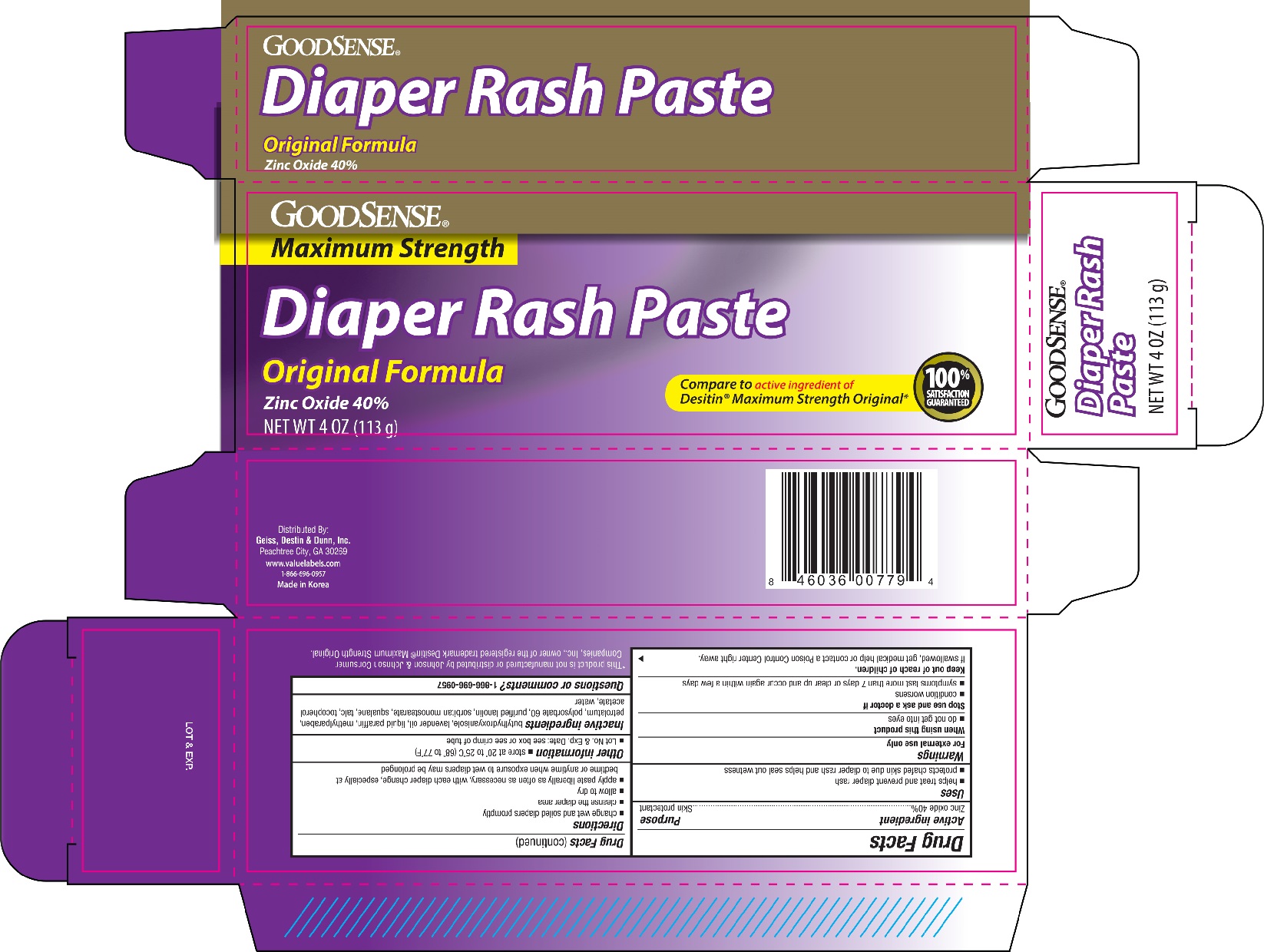 DRUG LABEL: Goodsense Diaper Rash
NDC: 50804-779 | Form: PASTE
Manufacturer: Geiss, Destin & Dunn, Inc.
Category: otc | Type: HUMAN OTC DRUG LABEL
Date: 20160105

ACTIVE INGREDIENTS: ZINC OXIDE 400 mg/1 g
INACTIVE INGREDIENTS: BUTYLATED HYDROXYANISOLE; LAVENDER OIL; PARAFFIN; METHYLPARABEN; PETROLATUM; POLYSORBATE 60; LANOLIN; SORBITAN MONOSTEARATE; SQUALANE; TALC; ALPHA-TOCOPHEROL ACETATE; WATER

Active ingredient Purpose

Zinc oxide 40%......................................................... Skin protectant

Uses

- helps treat and prevent diaper rash
- protects chafed skin due to diaper rash and helps seal out wetness

Warnings

For external use only

When using this product

- do not get into eyes

Stop use and ask a doctor if

- condition worsens
- symptoms last more than 7 days or clear up and occur again within a few days

Keep out of reach of children.

If swallowed, get medical help or contact a Poison Control Center right away.

Directions

- change wet and soiled diapers promptly
- cleanse the diaper area
- allow to dry
- apply paste liberally as often as necessary, with each diaper change, especially at bedtime or anytime when exposure to wet diapers may be prolonged

Other information

- store at 20° to 25°C (68° to 77°F)
- Lot No. & Exp. Date: see box or see crimp of tube

INACTIVE INGREDIENT

Inactive ingredients butylhydroxyanisole, lavender oil, liquid paraffin, methylparaben, petrolatum, polysorbate 60, purified lanolin, sorbitan monostearate, squalane, talc, tocopherol, acetate, water

DOSAGE AND ADMINISTRATION

Distributed by:

Geiss, Destin & Dunn, Inc.

Peachtree City, GA 30269

www.valuelabels.com

Made in Korea